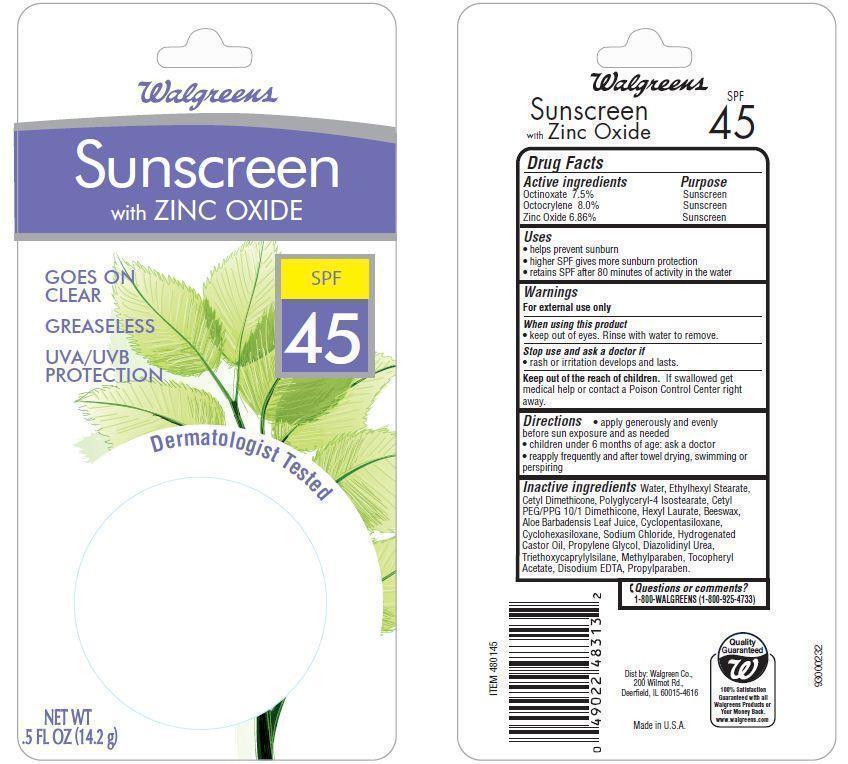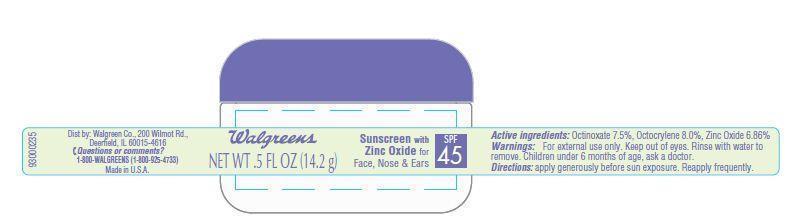 DRUG LABEL: Walgreens SunscreenSPF 45
          SPF 45
          
NDC: 0363-4008 | Form: LOTION
Manufacturer: WALGREEN CO.
Category: otc | Type: HUMAN OTC DRUG LABEL
Date: 20121204

ACTIVE INGREDIENTS: OCTOCRYLENE 8 g/100 g; ZINC OXIDE 6.86 g/100 g; OCTINOXATE 7.5 g/100 g
INACTIVE INGREDIENTS: WATER; ETHYLHEXYL STEARATE; POLYGLYCERYL-4 ISOSTEARATE; HEXYL LAURATE; YELLOW WAX ; ALOE VERA LEAF; CYCLOMETHICONE 5; SODIUM CHLORIDE; HYDROGENATED CASTOR OIL; METHYLPARABEN; EDETATE DISODIUM; PROPYLENE GLYCOL; DIAZOLIDINYL UREA; TRIETHOXYCAPRYLYLSILANE; .ALPHA.-TOCOPHEROL ACETATE; PROPYLPARABEN; CYCLOMETHICONE 6

Drug Facts

Active ingredients

Octinoxate 7.5%
Octocrylene 8.0%
Zinc Oxide 6.86%

Purpose

Sunscreen

Uses

- helps prevent sunburn
- higher SPF gives more sunburn protection
- retains SPF after 80 minutes of activity in the water

Warnings

For external use only

When using this product

- keep out of eyes.Rinse with water to remove.

stop use and ask a doctor if

- rash or irritation develops and lasts.

Keep out of the reach of children.

If swallowed get medical help or contact a Poison Control Center right away.

Directions

- apply generously and evenly before sun exposure and as needed
- Children under 6 months of age:ask a doctor
- reapply frequently and after towel drying, swimming or perspiring

Inactive Ingredients

Water, Ethylhexyl Stearate, Cetyl Dimethicone, Polyglyceryl-4 Isostearate, Cetyl PEG/PPG-10/1 Dimethicone, Hexyl Laurate, Beeswax, Aloe Barbadensis Leaf Juice, Cyclopentasiloxane, Cyclohexasiloxane, Sodium Chloride, Hydrogenated Castor Oil, Propylene Glycol, Diazolidnyl Urea, Triethoxycaprylylsilane, Methylparaben, Tocopheryl Acetate, Disodium EDTA, Propylparaben.

Principal Display Panel

Walgreens
Sunscreen
with ZINC OXIDE
SPF
45
GOES ON
CLEAR
GREASLESS
UVA/UVB
PROTECTION
Dermatologist Tested
NET WT
5 FL OZ (14.2 g)